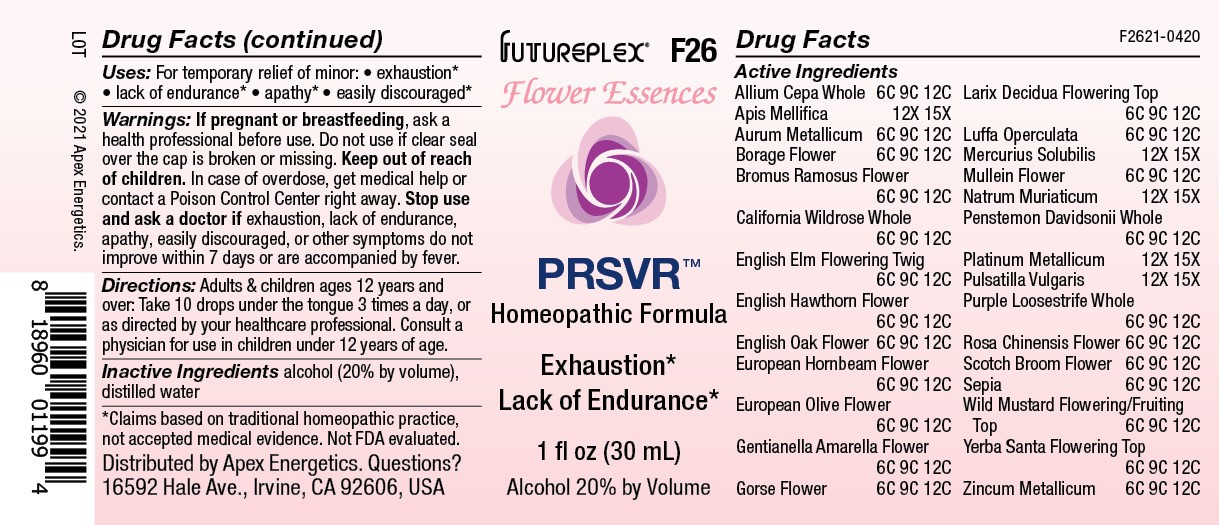 DRUG LABEL: F26
NDC: 63479-0626 | Form: SOLUTION/ DROPS
Manufacturer: Apex Energetics Inc.
Category: homeopathic | Type: HUMAN OTC DRUG LABEL
Date: 20240108

ACTIVE INGREDIENTS: ZINC 12 [hp_C]/1 mL; GOLD 12 [hp_C]/1 mL; ERIODICTYON CALIFORNICUM FLOWERING TOP 12 [hp_C]/1 mL; ALLIUM CEPA WHOLE 12 [hp_C]/1 mL; MERCURIUS SOLUBILIS 15 [hp_X]/1 mL; VERBASCUM DENSIFLORUM FLOWER 12 [hp_C]/1 mL; PLATINUM 15 [hp_X]/1 mL; ROSA CHINENSIS FLOWER 12 [hp_C]/1 mL; SODIUM CHLORIDE 15 [hp_X]/1 mL; GENTIANELLA AMARELLA FLOWER 12 [hp_C]/1 mL; ULEX EUROPAEUS FLOWER 12 [hp_C]/1 mL; LARIX DECIDUA FLOWERING TOP 12 [hp_C]/1 mL; LUFFA OPERCULATA FRUIT 12 [hp_C]/1 mL; PENSTEMON DAVIDSONII WHOLE 12 [hp_C]/1 mL; PULSATILLA VULGARIS 15 [hp_X]/1 mL; ROSA CALIFORNICA WHOLE 12 [hp_C]/1 mL; ULMUS PROCERA FLOWERING TWIG 12 [hp_C]/1 mL; CRATAEGUS MONOGYNA FLOWER 12 [hp_C]/1 mL; OLEA EUROPAEA FLOWER 12 [hp_C]/1 mL; SEPIA OFFICINALIS JUICE 12 [hp_C]/1 mL; SINAPIS ARVENSIS FLOWERING/FRUITING TOP 12 [hp_C]/1 mL; QUERCUS ROBUR FLOWER 12 [hp_C]/1 mL; LYTHRUM SALICARIA WHOLE 12 [hp_C]/1 mL; CYTISUS SCOPARIUS FLOWER 12 [hp_C]/1 mL; APIS MELLIFERA 15 [hp_X]/1 mL; BORAGO OFFICINALIS FLOWER 12 [hp_C]/1 mL; BROMUS RAMOSUS FLOWER 12 [hp_C]/1 mL; CARPINUS BETULUS FLOWER 12 [hp_C]/1 mL
INACTIVE INGREDIENTS: ALCOHOL; WATER

F26

Active Ingredients
Allium Cepa Whole | 6C 9C 12C
Apis Mellifica | 12X 15X
Aurum Metallicum | 6C 9C 12C
Borage Flower | 6C 9C 12C
Bromus Ramosus Flower | 6C 9C 12C
California Wildrose Whole | 6C 9C 12C
English Elm Flowering Twig | 6C 9C 12C
English Hawthron Flower | 6C 9C 12C
English Oak Flower | 6C 9C 12C
European Hornbeam Flower | 6C 9C 12C
European Olive Flower | 6C 9C 12C
Gentianella Amarella Flower | 6C 9C 12C
Gorse Flower | 6C 9C 12C
Larix Decidua Flowering Top | 6C 9C 12C
Luffa Operculata | 6C 9C 12C
Mercurius Solubilis | 12X 15X
Mullein Flower | 6C 9C 12C
Natrum Muriaticum | 12X 15X
Penstemon Davidsonii Whole | 6C 9C 12C
Platinum Metallicum | 12X 15X
Pulsatilla Vulgaris | 12X 15X
Purple Loosestrife Whole | 6C 9C 12C
Rosa Chinensis Flower | 6C 9C 12C
Scotch Broom Flower | 6C 9C 12C
Sepia | 6C 9C 12C
Wild Mustard Flowering/Fruiting Top | 6C 9C 12C
Yerba Santa Flowering Top | 6C 9C 12C
Zincum Metallicum | 6C 9C 12C

INDICATIONS AND USAGE

Uses:

For temporary relief of minor:

exhaustion*

lack of endurance*

apathy*

easily discouraged*

*Claims based on traditional homeopathic practice, not accepted medical evidence. Not FDA evaluated.

Warnings:

PREGNANCY OR BREAST FEEDING

If pregnant or breastfeeding, ask a health professional before use.

Do not use if clear seal over the cap is broken or missing.

Keep out of reach of children. In case of overdose, get medical help or contact a Poison Control Center right away.

Stop use and ask a doctor if eexhaustion, lack of endurance, apathy, easily discouraged, or other symptoms do not improve within 7 days or are accompanied by fever.

Directions:

Adults & children ages 12 years and over: Take 10 drops under the tongue 3 times a day, or as directed by your healthcare professional. Consult a physician for use in children under 12 years of age.

Inactive Ingredients

alcohol (20% by volume), distilled water

Distributed by Apex Energetics. Questions?

16592 Hale Ave., Irvine, CA 92606, USA

PACKAGE LABEL

FUTUREPLEX® F26

Flower Essences

PRSVR™

Homeopathic Formula

Exhaustion*

Lack of Endurance*

1 fl oz (30 mL)

Alcohol 20% by Volume